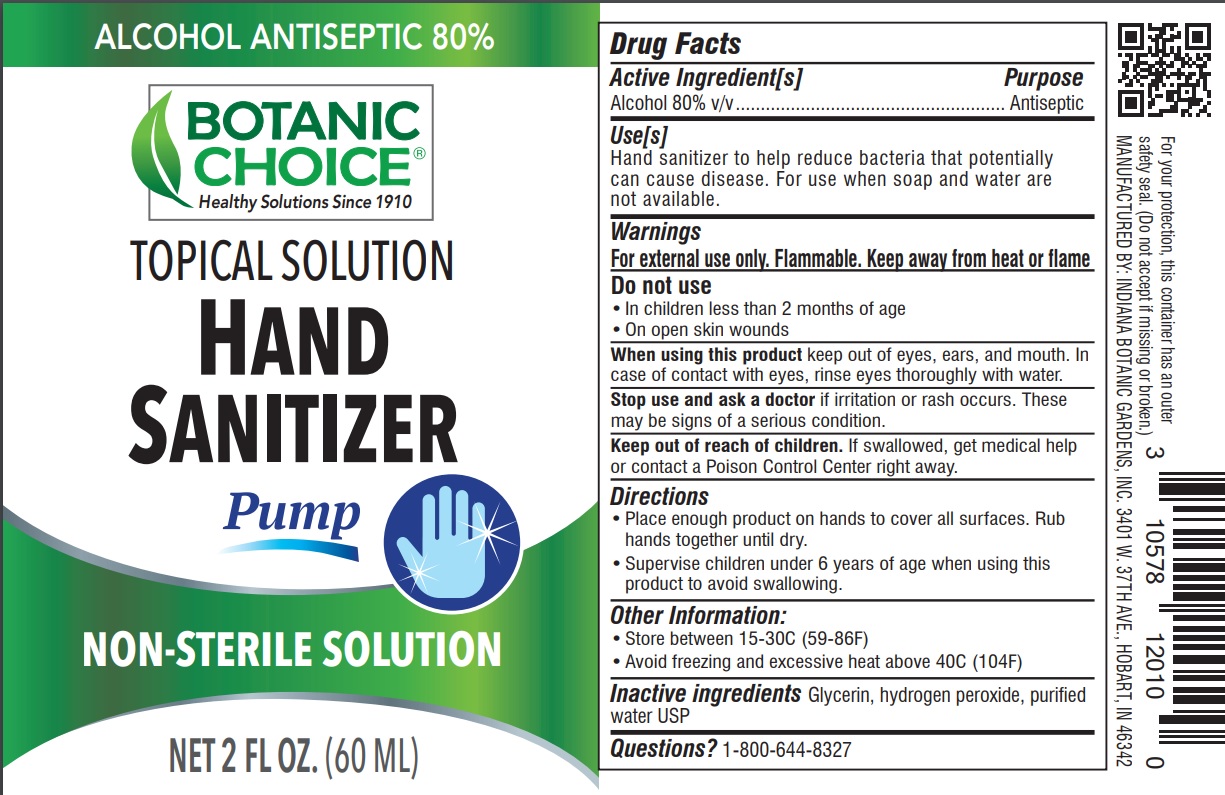 DRUG LABEL: Hand Sanitizer
NDC: 10578-120 | Form: LIQUID
Manufacturer: Indiana Botanic Gardens
Category: otc | Type: HUMAN OTC DRUG LABEL
Date: 20200429

ACTIVE INGREDIENTS: ALCOHOL 80 mL/100 mL
INACTIVE INGREDIENTS: GLYCERIN; HYDROGEN PEROXIDE; WATER

Hand Sanitizer

Active Ingredient

Alcohol 80% v/v

Purpose

Antiseptic

Use

Hand sanitizer to help reduce bacteria that potentially can cause disease. For use when soap and water are not available.

Warnings

For external use only. Flammable. Keep away from heat or flame

Do not use

• In children less than 2 months of age

• On open skin wounds

When using this product

keep out of eyes, ears, and mouth. In case of contact with eyes, rinse eyes thoroughly with water.

Stop use and ask a doctor

if irritation or rash occurs. These may be signs of a serious condition.

Keep out of reach of children

If swallowed, get medical help or contact a Poison Control Center right away

Directions

• Place enough product on hands to cover all surfaces. Rub hands together until dry.

• Supervise children under 6 years of age when using this product to avoid swallowing.

Other Information

• Store between 15-30C (59-86F)

• Avoid freezing and excessive heat above 40C (104F)

Inactive ingredients

Glycerin, hydrogen peroxide, purified water USP

Questions?

1-800-644-8327

For your protection, this container has an outer safety seal. (Do not accept if missing or broken.)

MANUFACTURED BY: INDIANA BOTANIC GARDENS, INC. 3401 W. 37TH AVE., HOBART, IN 46342

PACKAGE LABEL

ALCOHOL ANTISEPTIC 80%

Botanic Choice

Healthy Solutions Since 1910

Topical Solution

Hand Sanitizer

Pump

Non-sterile solution

Net 2 fl oz. (60 mL)